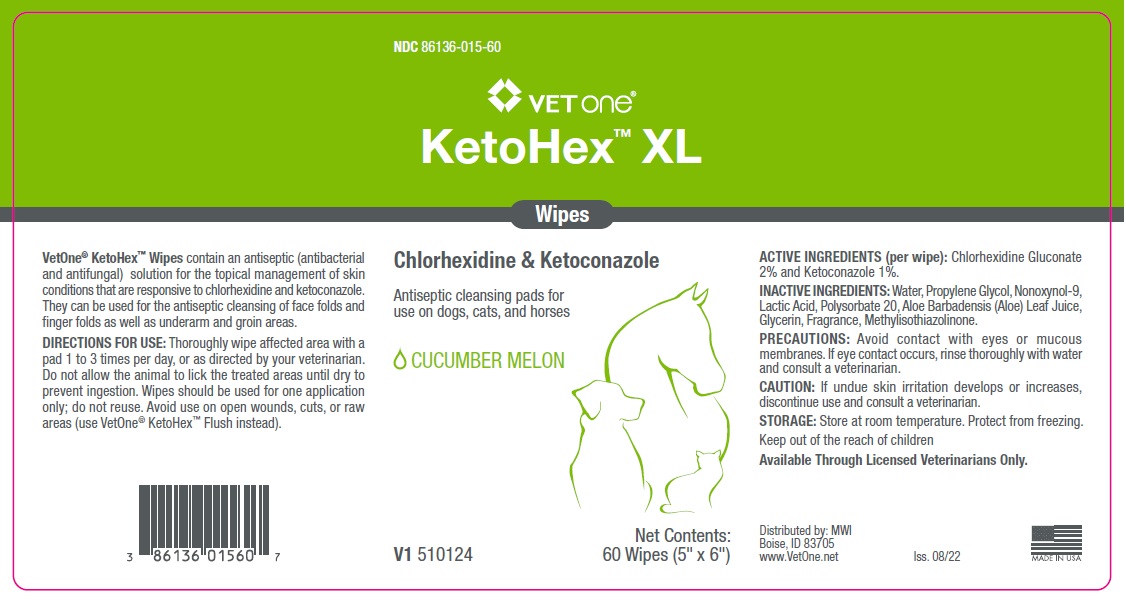 DRUG LABEL: VET one KetoHex XL Wipes
NDC: 86136-015 | Form: CLOTH
Manufacturer: MWI Animal Health
Category: animal | Type: OTC ANIMAL DRUG LABEL
Date: 20220826

ACTIVE INGREDIENTS: CHLORHEXIDINE GLUCONATE 2 g/100 mL; KETOCONAZOLE 1 g/100 mL
INACTIVE INGREDIENTS: WATER; PROPYLENE GLYCOL; NONOXYNOL-9; LACTIC ACID, UNSPECIFIED FORM; POLYSORBATE 20; ALOE VERA LEAF; GLYCERIN; METHYLISOTHIAZOLINONE

VET one® KetoHex™ XL Wipes

ACTIVE INGREDIENTS (per wipe):

Chlorhexidine Gluconate 2% and Ketoconazole 1%.

INACTIVE INGREDIENTS:

Water, Propylene Glycol, Nonoxynol-9, Lactic Acid, Polysorbate 20, Aloe Barbadensis (Aloe) Leaf Juice, Glycerin, Fragrance, Methylisothiazolinone.

PRECAUTIONS:

Avoid contact with eyes or mucous membranes. If eye contact occurs, rinse thoroughly with water and consult a veterinarian.

CAUTION:

If undue skin irritation develops or increases, discontinue use and consult a veterinarian.

STORAGE:

Store at room temperature. Protect from freezing.

Keep out of the reach of children

INDICATIONS AND USAGE

VetOne® KetoHex™ Wipes contain an antiseptic (antibacterial and antifungal) solution for the topical management of skin conditions that are responsive to chlorhexidine and ketoconazole. They can be used for the antiseptic cleansing of face folds and finger folds as well as underarm and groin areas.

DIRECTIONS FOR USE:

Thoroughly wipe affected area with a pad 1 to 3 times per day, or as directed by your veterinarian. Do not allow the animal to lick the treated areas until dry to prevent ingestion. Wipes should be used for one application only; do not reuse. Avoid use on open wounds, cuts, or raw areas (use VetOne® KetoHex™ Flush instead).

Antiseptic cleansing pads for use on dogs, cats, and horses

CUCUMBER MELON

Available Through Licensed Veterinarians Only.

Distributed by: MWI
Boise, ID 83705
www.VetOne.net

MADE IN USA